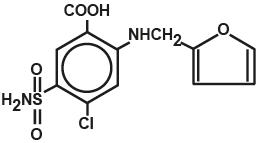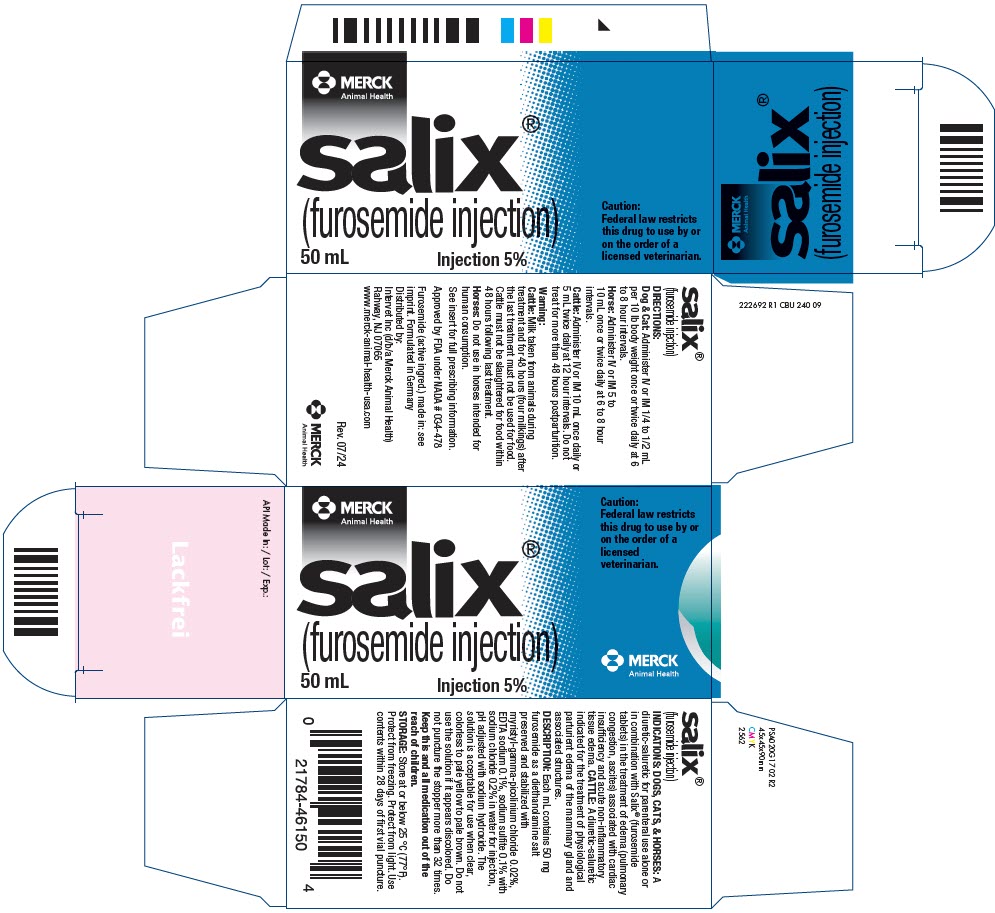 DRUG LABEL: Salix
NDC: 57926-465 | Form: INJECTION
Manufacturer: Merck Sharp & Dohme Corp.
Category: animal | Type: PRESCRIPTION ANIMAL DRUG LABEL
Date: 20241115

ACTIVE INGREDIENTS: FUROSEMIDE 50 mg/1 mL

SALIX®
(furosemide injection)

222690 R1

FOR VETERINARY USE ONLY

A diuretic-saluretic for prompt relief of edema.

Caution: Federal law restricts this drug to use by or on the order of a licensed veterinarian.

DESCRIPTION

Salix® (furosemide injection) is a chemically distinct diuretic and saluretic pharmacodynamically characterized by the following:

1) A high degree of efficacy, low-inherent toxicity and a high therapeutic index.
2) A rapid onset of action and of comparatively short duration.^1,2
3) A pharmacological action in the functional area of the nephron, i.e., proximal and distal tubules and the ascending limb of the loop of Henle.^2,3,4
4) A dose-response relationship and a ratio of minimum to maximum effective dose range greater than tenfold.^1,2
5) It may be administered orally or parenterally. It is readily absorbed from the intestinal tract and well tolerated.

The intravenous route produces the most rapid diuretic response.

The CAS Registry Number is 54-31-9.

Salix®, a diuretic, is an anthranilic acid derivative with the following structural formula:

Generic name: Furosemide (except in United Kingdom-furosemide). Chemical name: 4-chloro-N-furfuryl-5-sulfamoylanthranilic acid.

ACTIONS

The therapeutic efficacy of Salix® is from the activity of the intact and unaltered molecule throughout the nephron, inhibiting the reabsorption of sodium not only in the proximal and distal tubule but also in the ascending limb of the loop of Henle. The prompt onset of action is a result of the drug's rapid absorption and a poor lipid solubility. The low lipid solubility and a rapid renal excretion minimize the possibility of its accumulation in tissues and organs or crystalluria. Salix® has no inhibitory effect on carbonic anhydrase or aldosterone activity in the distal tubule. The drug possesses diuretic activity either in presence of acidosis or alkalosis.^1,2,3,4,5,6,7

INDICATIONS

Dogs, Cats & Horses:

Salix® is an effective diuretic possessing a wide therapeutic range. Pharmacologically it promotes the rapid removal of abnormally retained extracellular fluids. The rationale for the efficacious use of diuretic therapy is determined by the clinical pathology producing the edema. Salix® is indicated for the treatment of edema, (pulmonary congestion, ascites) associated with cardiac insufficiency and acute noninflammatory tissue edema.

The continued use of heart stimulants, such as digitalis or its glycosides is indicated in cases of edema involving cardiac insufficiency.

Cattle:

Salix® is indicated for the treatment of physiological parturient edema of the mammary gland and associated structures.

CONTRAINDICATIONS - PRECAUTIONS

Salix® is a highly effective diuretic-saluretic which if given in excessive amounts may result in dehydration and electrolyte imbalance. Therefore, the dosage and schedule may have to be adjusted to the patient's needs. The animal should be observed for early signs of electrolyte imbalance, and corrective measures administered. Early signs of electrolyte imbalance are: increased thirst, lethargy, drowsiness or restlessness, fatigue, oliguria, gastro-intestinal disturbances and tachycardia. Special attention should be given to potassium levels. Salix® may lower serum calcium levels and cause tetany in rare cases of animals having an existing hypocalcemic tendency.^10,11,12,13,14

Although diabetes mellitus is a rarely reported disease in animals, active or latent diabetes mellitus may on rare occasions be exacerbated by Salix®. While it has not been reported in animals the use of high doses of salicylates, as in rheumatic diseases, in conjunction with Salix® may result in salicylate toxicity because of competition for renal excretory sites.

Transient loss of auditory capacity has been experimentally produced in cats following intravenous injection of excessive doses of Salix® at a very rapid rate.^15,16,17

Electrolyte balance should be monitored prior to surgery in patients receiving Salix®. Imbalances must be corrected by administration of suitable fluid therapy.

Salix® is contraindicated in anuria. Therapy should be discontinued in cases of progressive renal disease if increasing azotemia and oliguria occur during the treatment. Sudden alterations of fluid and electrolyte imbalance in an animal with cirrhosis may precipitate hepatic coma, therefore observation during period of therapy is necessary. In hepatic coma and in states of electrolyte depletion, therapy should not be instituted until the basic condition is improved or corrected. Potassium supplementation may be necessary in cases routinely treated with potassium-depleting steroids.

WARNINGS

Salix® is a highly effective diuretic and if given in excessive amounts as with any diuretic may lead to excessive diuresis which could result in electrolyte imbalance, dehydration and reduction of plasma volume enhancing the risk of circulatory collapse, thrombosis, and embolism. Therefore, the animal should be observed for early signs of fluid depletion with electrolyte imbalance, and corrective measures administered. Excessive loss of potassium in patients receiving digitalis or its glycosides may precipitate digitalis toxicity. Caution should be exercised in animals administered potassium-depleting steroids.

It is important to correct potassium deficiency with dietary supplementation. Caution should be exercised in prescribing enteric-coated potassium tablets.

There have been several reports in human literature, published and unpublished, concerning non-specific small-bowel lesions consisting of stenosis, with or without ulceration, associated with the administration of enteric-coated thiazides with potassium salts. These lesions may occur with enteric-coated potassium tablets alone or when they are used with nonenteric-coated thiazides, or certain other oral diuretics. These small-bowel lesions may have caused obstruction, hemorrhage, and perforation. Surgery was frequently required, and deaths have occurred. Available information tends to implicate enteric-coated potassium salts, although lesions of this type also occur spontaneously. Therefore, coated potassium-containing formulations should be administered only when indicated and should be discontinued immediately if abdominal pain, distention, nausea, vomiting, or gastro-intestinal bleeding occurs.

Human patients with known sulfonamide sensitivity may show allergic reactions to Salix®; however, these reactions have not been reported in animals.

Sulfonamide diuretics have been reported to decrease arterial responsiveness to pressor amines and to enhance the effect of tubocurarine. Caution should be exercised in administering curare or its derivatives to patients undergoing therapy with Salix® and it is advisable to discontinue Salix® for one day prior to any elective surgery.

WARNING

CATTLE: Milk taken from animals during treatment and for 48 hours (four milkings) after the last treatment must not be used for food. Cattle must not be slaughtered for food within 48 hours following last treatment.

HORSES: Do not use in horses intended for human consumption.

DOSAGE AND ADMINISTRATION

The usual dosage of Salix® is 1 to 2 mg/lb. body weight (approximately 2.5 to 5 mg/kg). The lower dosage is suggested for cats. Administer once or twice daily at 6 to 8 hour intervals either orally, intravenously, or intramuscularly. A prompt diuresis usually ensues from the initial treatment. Diuresis may be initiated by the parenteral administration of Salix® Injection and then maintained by oral administration.

The dosage should be adjusted to the individual's response. In severe edematous or refractory cases, the dose may be doubled or increased by increments of 1 mg per pound body weight. The established effective dose should be administered once or twice daily. The daily schedule of administration can be timed to control the period of micturition for the convenience of the client or veterinarian. Mobilization of the edema may be most efficiently and safely accomplished by utilizing an intermittent daily dosage schedule, i.e., every other day or 2 to 4 consecutive days weekly.

Diuretic therapy should be discontinued after reduction of the edema, or maintained after determining a carefully programmed dosage schedule to prevent recurrence of edema. For long-term treatment, the dose can generally be lowered after the edema has once been reduced. Re-examination and consultations with client will enhance the establishment of a satisfactorily programmed dosage schedule. Clinical examination and serum BUN, CO2 and electrolyte determinations should be performed during the early period of therapy and periodically thereafter, especially in refractory cases. Abnormalities should be corrected or the drug temporarily withdrawn.

DOSAGE:

The solution is acceptable for use when clear, colorless to pale yellow to pale brown. Do not use this solution if it appears discolored. Do not puncture the stopper more than 32 times.

DOG AND CAT

Administer intramuscularly or intravenously 1/4 to 1/2 mL per 10 pounds body weight.

Administer once or twice daily, permitting a 6 to 8 hour interval between treatments. In refractory or severe edematous cases, the dosage may be doubled or increased by increments of 1 mg per pound body weight as recommended in preceding paragraphs, "Dosage and Administration".

HORSE

The individual dose is 250 mg to 500 mg (5 to 10 mL) administered intramuscularly or intravenously once or twice daily at 6 to 8 hour intervals until desired results are achieved. The veterinarian should evaluate the degree of edema present and adjust dosage schedule accordingly. Do not use in horses intended for human consumption.

CATTLE

The individual dose administered intramuscularly or intravenously is 500 mg (10 mL) once daily or 250 mg (5 mL) twice daily at 12 hour intervals. Treatment not to exceed 48 hours postparturition.

Milk taken from animals during treatment and for 48 hours (four milkings) after the last treatment must not be used for food. Cattle must not be slaughtered for food within 48 hours following last treatment.

HOW SUPPLIED/STORAGE AND HANDLING

Salix® (furosemide injection) 5% Each mL contains: 50 mg furosemide as a diethanolamine salt preserved and stabilized with myristyl-gamma-picolinium chloride 0.02%, EDTA sodium 0.1%, sodium sulfite 0.1% with sodium chloride 0.2% in distilled water, pH adjusted with sodium hydroxide.

Available in 50 mL multidose vials.

Storage Conditions:

Store at or below 25 °C (77°F). Protect from freezing. Protect from light. Use contents within 28 days of first vial puncture.

TOXICOLOGY

Acute Toxicity:

The following table illustrates low acute toxicity of Salix® in three different species.

(Two values indicate two different studies.)

LD50 of Salix® in mg/kg body weight
SPECIES | INTRAVENOUS
Mouse | 308
Rat | 680
Dog | >300 and >464
*NOTE: The lower value for the rat oral LD50 was obtained in a group of fasted animals; the higher figure is from a study performed in fed rats.

Toxic doses lead to convulsions, ataxia, paralysis and collapse. Animals surviving toxic dosages may become dehydrated and depleted of electrolytes due to the massive diuresis and saluresis.

Chronic Toxicity:

Chronic toxicity studies with Salix® were done in a one-year study in rats and dogs. In a one-year study in rats, renal tubular degeneration occurred with all doses higher than 50 mg/kg. A six-month study in dogs revealed calcification and scarring of the renal parenchyma at all doses above 10 mg/kg.

Reproductive Studies:

Reproductive studies were conducted in mice, rats and rabbits. Only in rabbits administered high doses (equivalent to 10 to 25 times the recommended average dose of 2 mg/kg for dogs, cats, horses, and cattle) of furosemide during the second trimester period did unexplained maternal deaths and abortions occur. The administration of Salix® is not recommended during the second trimester of pregnancy.

REFERENCES

1. Timmerman, R.J.; Springman, F.R., and Thoms, R.K.: Evaluation of Furosemide, a New Diuretic Agent. Current Therapeutic Research 6(2):88-94, February 1964.
2. Muschaweck, R., and Hajdu, P.: Die salidiuretische Wirksamkeit der Chlor-N-(2-furylmethyl)-sulfamyl-anthranilsaure. Arzneimittel-Forschung 14:44-47, 1964. (The Saluretic Action of 4-Chloro-N-(2-furylmethyl)-5-sulfamyl-anthranilic acid).
3. Suki, W.; Rector, Jr., F.C., and Seldin, D.W.: The Site of Action of Furosemide and Other Sulfonamide Diuretics in the Dog. Journal of Clinical Investigation 44(9): 1458-1469,1965.
4. Deetjen, P.: Mikropunktionsunter-suchungen zur Wirkung von Furosemid. Pflugers Archiv fuer die Gesamte Physiologie 284:184-190, 1965 (Micropuncture Studies of the Action of Furosemide).
5. Berman, L.B., and Ebrahimi, A.: Experiences with Furosemide in Renal Disease. Proceedings of the Society for Experimental Biology and Medicine 188:333-336, February 1965.
6. Schmidt, H.A.E.: "Animal Experiments with S35 Tagged Lasix® in Canine and Ovine." Radio-chemical Pharmacological Laboratory, Farbwerke Hoechst, Frankfurt, West Germany.
7. Haussler, A., and Hajdu, P.: "Methods Biological Identification and Results of Studies on Absorption, Elimination and Metabolism." Research Laboratories, Farbwerke Hoechst, Frankfurt, West Germany.
8. Wilson, A.F., and Simmons, D.H.: Diuretic Action in Hypochloremic Dogs. Clinical Research 14(1):158, January 1966.
9. Hook, J.B., and Williamson, H.E.: Influence of Probenecid and Alterations in Acid-Base Balance of the Saluretic Activity of Furosemide. Journal of Pharmacology and Experimental Therapeutics: 149(3):404-408, 1965.
10. Antoniou, L.D.; Eisner, G.M.; Slotkoff, L.M. and Lilienfield, L.S.: Sodium and Calcium Transport in the Kidney. Clinical Research 15(4):476, December 1967.
11. Duarte, C.G.: Effects of Furosemide (F) and Ethacrynic Acid (ETA) on the Renal Clearance of Phosphate (Cp), Ultrafilterable Calcium (CUfCa) and Magnesium (CUfMg). Clinical Research 15(2):357, April 1967.
12. Duarte, C.G.: Effects of Ethacrynic Acid and Furosemide on Urinary Calcium, Phosphate and Magnesium. Metabolism 17:867-876, October 1968.
13. Nielsen, S.P.; Andersen, O., and Steven, K.E.: Magnesium and Calcium Metabolism during Prolonged Furosemide (Lasix®) Administration to Normal Rats. Acta Pharmacol. et Toxicol. 1969, 27:469-479.
14. Reimold, E.W.: The effect of Furosemide on Hypercalcemia Due to Dihydrotachysterol. Metabolism 21(7), July 1972.
15. Brown, R.D., and McElwee, Jr., T.W.: Effects of Intra-Arterially and Intravenously Administered Ethacrynic Acid and Furosemide on Cochlear N, in Cats. Toxicology and Applied Pharmacology 22: 589-594, 1972.
16. Mathog, R.H.; Thomas, W.G., and Hudson, W.R.: Ototoxicity of New and Potent Diuretics. Archives of Otolaryngology 92(l):7-13, July 1970.
17. Mathog, R.H., and Matz, G.J.: Ototoxic Effects of Ethacrynic Acid. Annals of Otolaryngology Vol. 81, 1972.

Distributed by:
Intervet Inc (d/b/a Merck Animal Health)
Rahway, NJ 07065

Salix® Injection 5%
Formulated in Germany by:
Intervet International GmbH

Approved by FDA under NADA # 034-478
www.merck-animal-health-usa.com

Rev. 07/24

PRINCIPAL DISPLAY PANEL - 50 mL Vial Carton

MERCK
Animal Health

salix®
(furosemide injection)

50 mL
Injection 5%

Caution:
Federal law restricts
this drug to use by or
on the order of a
licensed
veterinarian.

MERCK
Animal Health